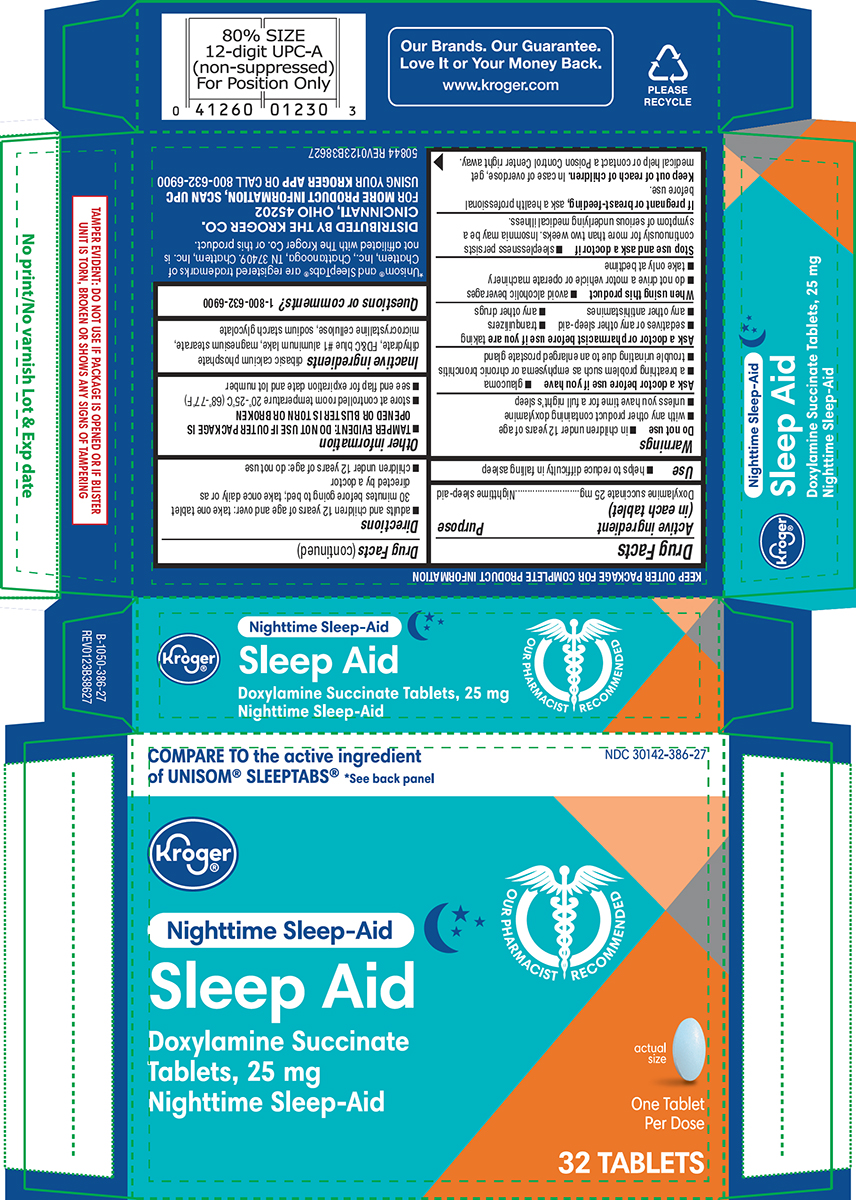 DRUG LABEL: Sleep Aid
NDC: 30142-386 | Form: TABLET
Manufacturer: Kroger Company
Category: otc | Type: HUMAN OTC DRUG LABEL
Date: 20250822

ACTIVE INGREDIENTS: DOXYLAMINE SUCCINATE 25 mg/1 1
INACTIVE INGREDIENTS: DIBASIC CALCIUM PHOSPHATE DIHYDRATE; FD&C BLUE NO. 1 ALUMINUM LAKE; MAGNESIUM STEARATE; MICROCRYSTALLINE CELLULOSE; SODIUM STARCH GLYCOLATE TYPE A POTATO

Kroger 44-386 Delisted

Active ingredient (in each tablet)

Doxylamine succinate 25 mg

Purpose

Nighttime sleep-aid

Use

- helps to reduce difficulty in falling asleep

Warnings

Do not use

- in children under 12 years of age
- with any other product containing doxylamine
- unless you have time for a full night’s sleep

Ask a doctor before use if you have

- glaucoma
- a breathing problem such as emphysema or chronic bronchitis
- trouble urinating due to an enlarged prostate gland

Ask a doctor or pharmacist before use if you are

taking

- sedatives or any other sleep-aid
- tranquilizers
- any other antihistamines
- any other drugs

When using this product

- avoid alcoholic beverages
- do not drive a motor vehicle or operate machinery
- take only at bedtime

Stop use and ask a doctor if

- sleeplessness persists continuously for more than two weeks. Insomnia may be a symptom of serious underlying medical illness.

If pregnant or breast-feeding,

ask a health professional before use.

Keep out of reach of children.

In case of overdose, get medical help or contact a Poison Control Center right away.

Directions

- adults and children 12 years of age and over: take one tablet 30 minutes before going to bed; take once daily or as directed by a doctor
- children under 12 years of age: do not use

Other information

- TAMPER EVIDENT: DO NOT USE IF OUTER PACKAGE IS OPENED OR BLISTER IS TORN OR BROKEN
- store at controlled room temperature 20°-25°C (68°-77°F)
- see end flap for expiration date and lot number

Inactive ingredients

dibasic calcium phosphate dihydrate, FD&C blue #1 aluminum lake, magnesium stearate, microcrystalline cellulose, sodium starch glycolate

Questions or comments?

1-800-632-6900

Principal Display Panel

COMPARE TO the active ingredient
of UNISOM® SLEEPTABS®*See back panel

NDC 30142-386-27

Kroger®

Nighttime Sleep-Aid

OUR PHARMACIST RECOMMENDED

Sleep Aid
Doxylamine Succinate
Tablets, 25 mg
Nighttime Sleep-Aid

actual
size

One Tablet
Per Dose

32 TABLETS

TAMPER EVIDENT: DO NOT USE IF PACKAGE IS OPENED OR IF BLISTER
UNIT IS TORN, BROKEN OR SHOWS ANY SIGNS OF TAMPERING

*Unisom® and SleepTabs® are registered trademarks of
Chattem, Inc., Chattanooga, TN 37409. Chattem, Inc. is
not affiliated with The Kroger Co. or this product.

DISTRIBUTED BY THE KROGER CO.
CINCINNATI, OHIO 45202
FOR MORE PRODUCT INFORMATION, SCAN UPC
USING YOUR KROGER APP OR CALL 800-632-6900

50844 REV0123B38627

Our Brands. Our Guarantee.
Love It or Your Money Back.
www.kroger.com

PLEASE
RECYCLE

Kroger 44-386